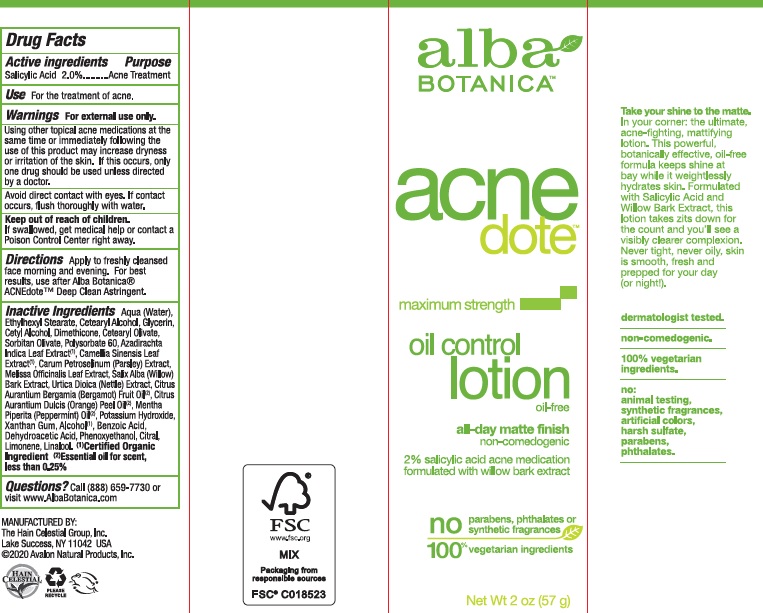 DRUG LABEL: Alba Botanica Acnedote Oil Control
NDC: 61995-2062 | Form: LOTION
Manufacturer: The Hain Celestial Group, Inc.
Category: otc | Type: HUMAN OTC DRUG LABEL
Date: 20241128

ACTIVE INGREDIENTS: SALICYLIC ACID 2 g/100 g
INACTIVE INGREDIENTS: ORANGE OIL; BERGAMOT OIL; URTICA DIOICA LEAF; WILLOW BARK; AZADIRACHTA INDICA LEAF; GREEN TEA LEAF; PARSLEY; WATER; CETOSTEARYL ALCOHOL; GLYCERIN; SORBITAN OLIVATE; POLYSORBATE 60; POTASSIUM HYDROXIDE; ALCOHOL; BENZOIC ACID; DEHYDROACETIC ACID; MELISSA OFFICINALIS LEAF; ETHYLHEXYL STEARATE; CETYL ALCOHOL; DIMETHICONE; CETEARYL OLIVATE; XANTHAN GUM; PHENOXYETHANOL; PEPPERMINT OIL

AcneDote Oil Control Lotion

ACTIVE INGREDIENTS

Salicylic Acid 2.0%

USE

- For the treatment of acne
- Apply to freshly cleansed face morning and evening
- For the best results, use after Alba Botanica Natural ACNEdote Deep Clean Astringent

WARNINGS

For external use only.

Avoid direct contact with eyes. If contact occurs, flush thoroughly with water.

PURPOSE

Acne Treatment

Keep out of reach of children. If swallowed, get medical help or contact a Poison Control Center right away

INACTIVE INGREDIENT

water, Ethylhexyl Stearate,Cetearyl Alcohol, Glycerin, Cetyl Alcohol, Dimethicone, Cetearyl Olivate, Sorbitan Olivate, Polysorbate 60, Azadirachta Indica Leaf Extract (1), Camellia Sinensis Leaf Extract (1), Carum Petroselinum (Parsley) Extract, Melissa Officinalis Leaf Extract, Salix Alba (Willow) Bark Extract, Urtica Dioica (Nettle) Extract, Citrus Aurantium Bergamia (Bergamot) Fruit Oil (2), Citrus Aurantium Dulcis (Orange) Peel Oil (2), Mentha Piperita (Peppermint) Oil (2), Potassium Hydroxide, Xanthan Gum, Alcohol (1), Benzoic Acid, Dehydroacetic Acid, Phenoxyethanol.

(1) Certified Organic Ingredient; ((2) For scent only

DOSAGE AND ADMINISTRATION

Using other topical acne medications at the same time or immediately following the use of this product may increase dryness or irritation of the skin. If this occurs,only one drug should be used unless directed by a doctor.